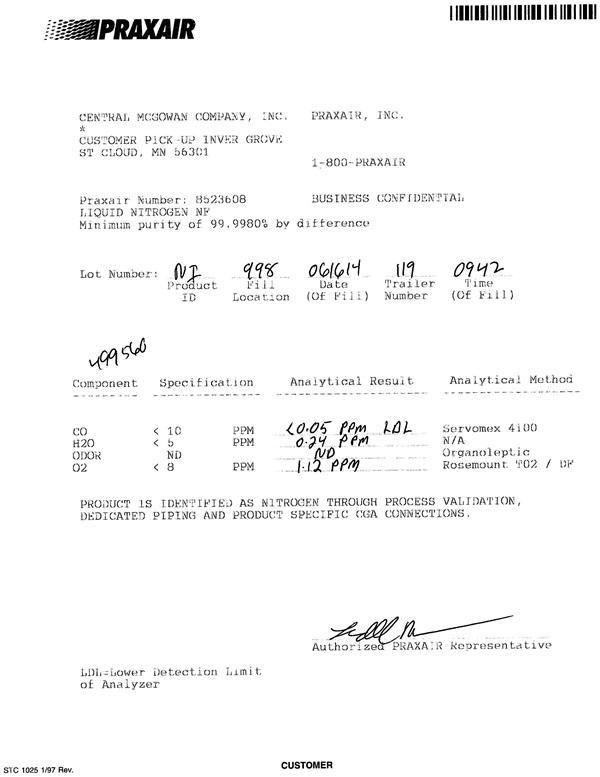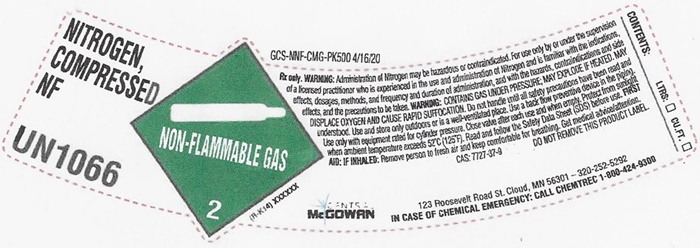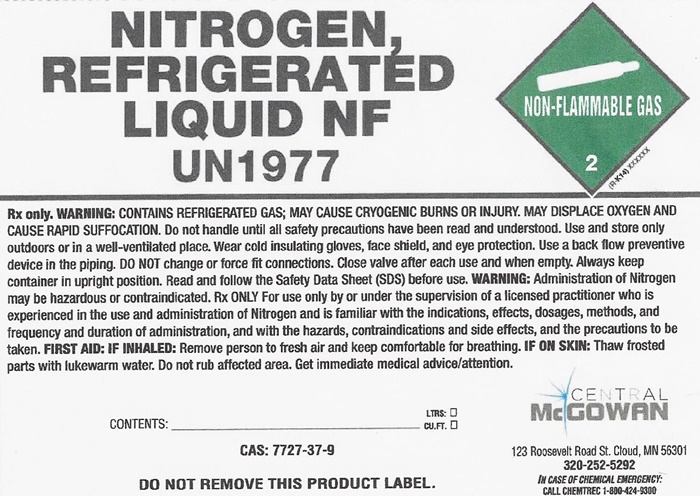 DRUG LABEL: NITROGEN
NDC: 10221-002 | Form: GAS
Manufacturer: Central-McGowan, Inc.
Category: prescription | Type: HUMAN PRESCRIPTION DRUG LABEL
Date: 20241104

ACTIVE INGREDIENTS: NITROGEN 99 L/100 L

Nitrogen

NITROGEN NF COA

PRAXAIR

CENTRAL MCGOWAN COMPANY, INC. PRAXAIR, INC.

CUSTOMER PICK-UP INVER GROVE

ST CLOUD, MN 56301 1-800-PRAXAIR

Praxair Number: 8523608 BUSINESS CONFIDENTIAL

LIQUID NITROGEN NF

Minimum purity of 99.9980% by difference

Lot Number: NI 998 061614 119 0942

Product Fill Date Trailer Time

ID Location (Of Fill) Number (Of Fill)

Component Specification Analytical Result Analytical Method

CO <10 ppm <0.05 ppm LDL Servomex 4100

H20 <5 ppm 0.24 ppm N/A

ODOR ND ND Organoleptic

O2 <8 ppm 1.12 ppm Rosemount TO2 /DP

PRODUCT IS IDENTIFIED AS NITROGEN THROUGH PROCESS VALIDATION, DEDICATED PIPING AND PRODUCT SPECIFIC CGA CONNECTIONS.

Authorized PRAXAIR Representative

LDL: Lower Detection Limit

Of Analyzer

STC 1025 1/97 Rev. CUSTOMER

NITROGEN, COMPRESSED NF UN1066

NON-FLAMMABLE GAS 2 (R-K14) XXXXXX

GCS-NNF-CMG-PK500 4/16/20

Rx only. WARNING: Administration of Nitrogen may be hazardous or contraindicated. For use only by or under the supervision of a licensed practioner who is experienced in the use and administration of Nitrogen and is familiar with the indications, effects, dosages, methods, and frequency and duration of administration, and with the hazards, contraindications and side effects and the precautions to be taken. WARNING: CONTAINS GAS UNDER PRESSURE; MAY EXPLODE, IF HEATED, MAY DISPLACE OXYGEN AND CAUSE RAPID SUFFOCCATION. Do not handle until all safety precautions have been read and understood. Use and store only outdoors or in a well-ventilated place. Use a back flow preventive device in the piping. Use only with equipment rated for cylinder pressure. Close valve after each use and when empty. Protect from sunlight when ambient temperature exceeds 52°C (125°F). Read and follow the Safety Data Sheet (SDS) before use. FIRST AID; IF INHALED; Remove person to fresh air and keep comfortable for breathing. Get medical advice/attention.

CAS: 7727-37-9 DO NOT REMOVE THIS PRODUCT LABEL

CENTRAL McGOWAN 123 Roosevelt Road St. Cloud, MN 56301 – 320-252-5292

In case of chemical emergency: call chemtrec 1-800-424-9300

CONTENTS: LTRS: □ CU FT. □

NITROGEN, REFRIGERATED LIQUID NF UN1977

NON-FLAMMABLE GAS 2 (R-K14) XXXXXX

Rx only. WARNING: CONTAINS REFRIGERATED GAS; MAY CAUSE CRYOGENIC BURNS OR INUURY. MAY DISPLACE OXYGEN AND CAUSE RAPID SUFFOCATION. Do not handle until all safety precautions have been read and understood. Use and store only outdoors or in a well-ventilated place. Wear cold insulating gloves, face shield, and eye protection. Use a backflow preventive device in the piping. DO NOT change or force fit connections. Close valve after each use and when empty. Always keep container in upright position. Read and follow the Safety Data Sheet (SDS) before use.

WARNING: Administration of Nitrogen may be hazardous or contraindicated. Rx ONLY For use only by or under the supervision of a licensed practitioner who is experienced in the use and administration of Nitrogen and is familiar with the indications, effects, dosages, methods, and frequency and duration of administration, and with the hazards, contraindications, and side effects, and the precautions to be taken.

FIRST AID: IF INHALED: Remove person to fresh air and keep comfortable for breathing. IF ON SKIN: Thaw frosted parts with lukewarm water. Do not rub affected area. Get immediate medical advice/attention.

CONTENTS: ________________________ LTRS: ___ CU FT: ___

CAS: 7727-37-9

DO NOT REMOVE THIS PRODUCT LABEL.

In case of emergencyinvolving this material call INFOTRAC at 1-800-535-5053

CENTRAL McGOWN

123 Roosevelt Road St. Cloud, MN 56301

320-252-5292

IN CASE OF CHEMICAL EMERGENCY

CALL CHEMTREC 1-800-424-9300